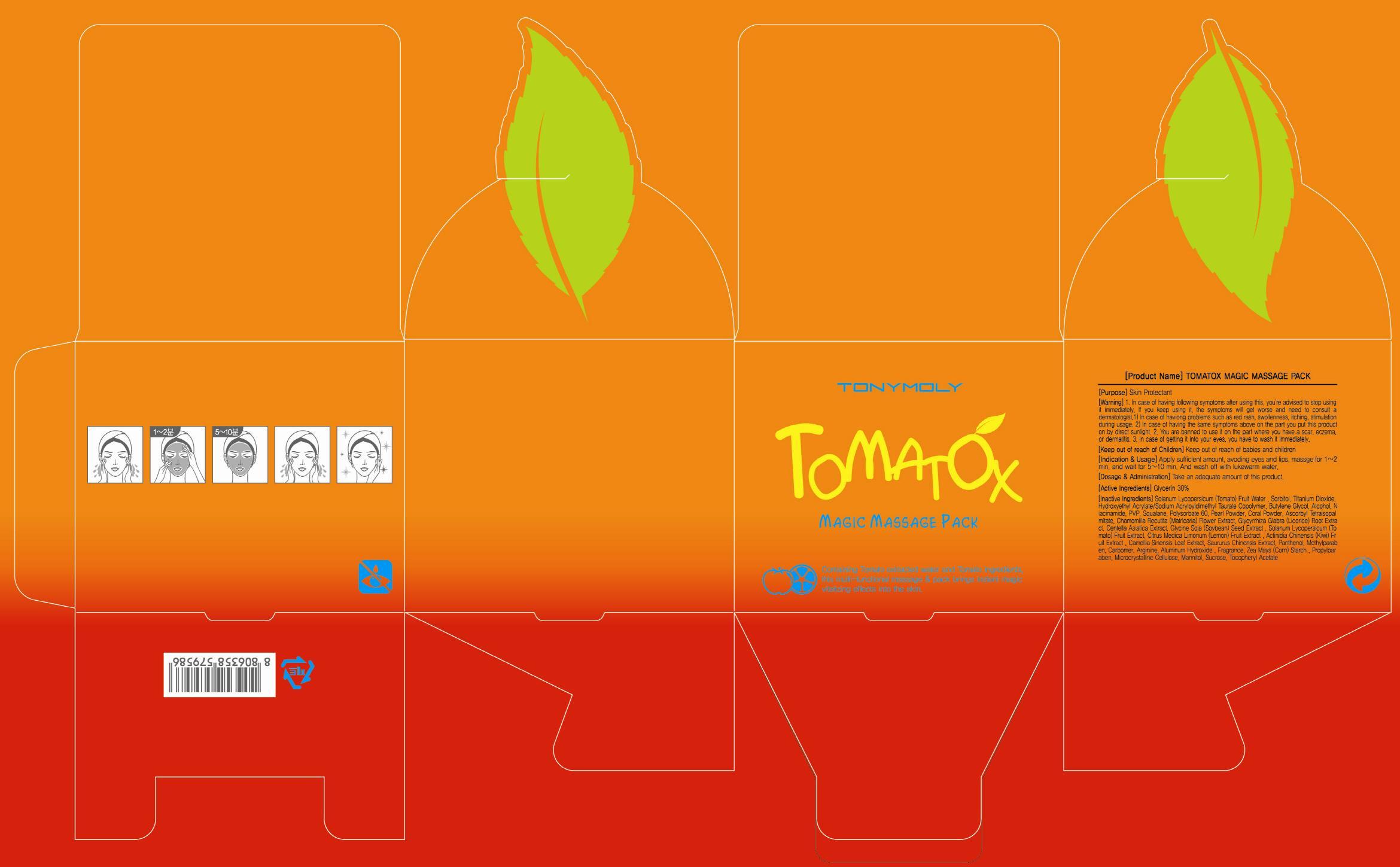 DRUG LABEL: Tomatox Magic Massage Pack
NDC: 59078-034 | Form: CREAM
Manufacturer: TONYMOLY CO., LTD.
Category: otc | Type: HUMAN OTC DRUG LABEL
Date: 20130729

ACTIVE INGREDIENTS: Glycerin 24 g/80 g
INACTIVE INGREDIENTS: TOMATO; Sorbitol

ACTIVE INGREDIENT

Active Ingredient: Glycerin 30%

INACTIVE INGREDIENT

Inactive Ingredients:
Solanum Lycopersicum (Tomato) Fruit Water, Sorbitol, Titanium Dioxide, Hydroxyethyl Acrylate/Sodium Acryloyldimethyl Taurate Copolymer, Butylene Glycol, Alcohol, Niacinamide, PVP, Squalane, Polysorbate 60, Pearl Powder, Coral Powder, Ascorbyl Tetraisopalmitate, Chamomilla Recutita (Matricaria) Flower Extract, Glycyrrhiza Glabra (Licorice) Root Extract, Centella Asiatica Extract, Glycine Soja (Soybean) Seed Extract , Solanum Lycopersicum (Tomato) Fruit Extract, Citrus Medica Limonum (Lemon) Fruit Extract , Actinidia Chinensis (Kiwi) Fruit Extract , Camellia Sinensis Leaf Extract, Saururus Chinensis Extract, Panthenol, Methylparaben, Carbomer, Arginine, Aluminum Hydroxide , Fragrance, Zea Mays (Corn) Starch , Propylparaben, Microcrystalline Cellulose, Mannitol, Sucrose, Tocopheryl Acetate

PURPOSE

PURPOSE: Skin Protectant

WARNINGS

1. In case of having following symptoms after using this, you're advised to stop using it immediately. If you keep using it, the symptoms will get worse and need to consult a dermatologist.
1) In case of having problems such as red rash, swollenness, itching, stimulation during usage.
2) In case of having the same symptoms above on the part you put this product on by direct sunlight.
2. You are banned to use it on the part where you have a scar, eczema, or dermatitis.
3. In case of getting it into your eyes, you have to wash it immediately.

KEEP OUT OF REACH OF CHILDREN

Keep out of reach of babies and children

INDICATIONS AND USAGE: Apply sufficient amount, avoding eyes and lips, massge for 1-2 min, and wait for 5-10 min. And wash off with lukewarm water.

DOSAGE AND ADMINISTRATION: Take an adequate amount of this product.